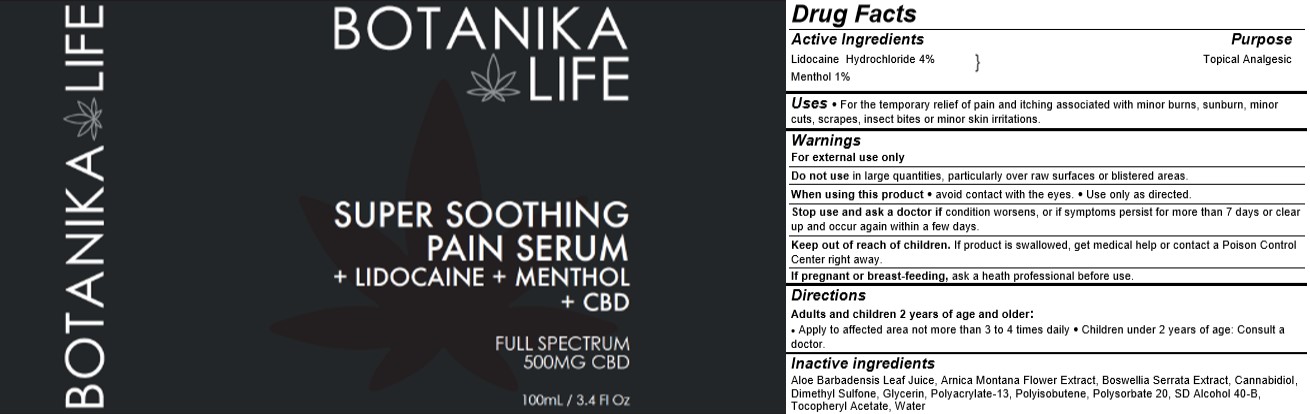 DRUG LABEL: Botanika Life
NDC: 58443-0391 | Form: LIQUID
Manufacturer: Prime Enterprises, Inc.
Category: otc | Type: HUMAN OTC DRUG LABEL
Date: 20210125

ACTIVE INGREDIENTS: LIDOCAINE HYDROCHLORIDE 38.44 mg/1 mL; MENTHOL 9.61 mg/1 mL
INACTIVE INGREDIENTS: DIMETHYL SULFONE; ALPHA-TOCOPHEROL ACETATE; WATER; POLYISOBUTYLENE (1000 MW); POLYSORBATE 20; ALCOHOL; INDIAN FRANKINCENSE; ALOE VERA LEAF; ARNICA MONTANA FLOWER; CANNABIDIOL; GLYCERIN

Botanika Life Super Soothing Pain Serum

Active Ingredients

Lidocaine Hydrochloride 4%

Menthol 1%

Purpose

Topical Analgesic

Uses

For the temporary relief of pain and itching associated with minor burns, sunburn, minor cuts, scrapes, insect bites or minor skin irritations.

Warnings

For external use only

Do not use

in large quantities, particularly over raw surfaces or blistered areas.

When using this product

avoid contact with the eyes.

Use only as directed.

Stop use and ask a doctor

if condition worsens, or if symptoms persist more than 7 days or clear up and occur again within a few days.

Keep out of reach of children.

If product is swallowed, get medical help or contact a Poison Control Center right away.

If pregnant or breast-feeding,

ask a health professional before use.

Directions

Adults and children 2 years of age and older:

Apply to affected area not more than 3 to 4 times daily

Children under 2 years of age: Consult a doctor.

Inactive ingredients

Aloe Barbadensis Leaf Juice, Arnica Montana Flower Extract, Boswellia Serrata Extract, Cannabidiol, Dimethyl Sulfone, Glycerin, Polyacrylate-13, Polyisobutene, Polysorbate 20, SD Alcohol 40-B, Tocopheryl Acetate, Water